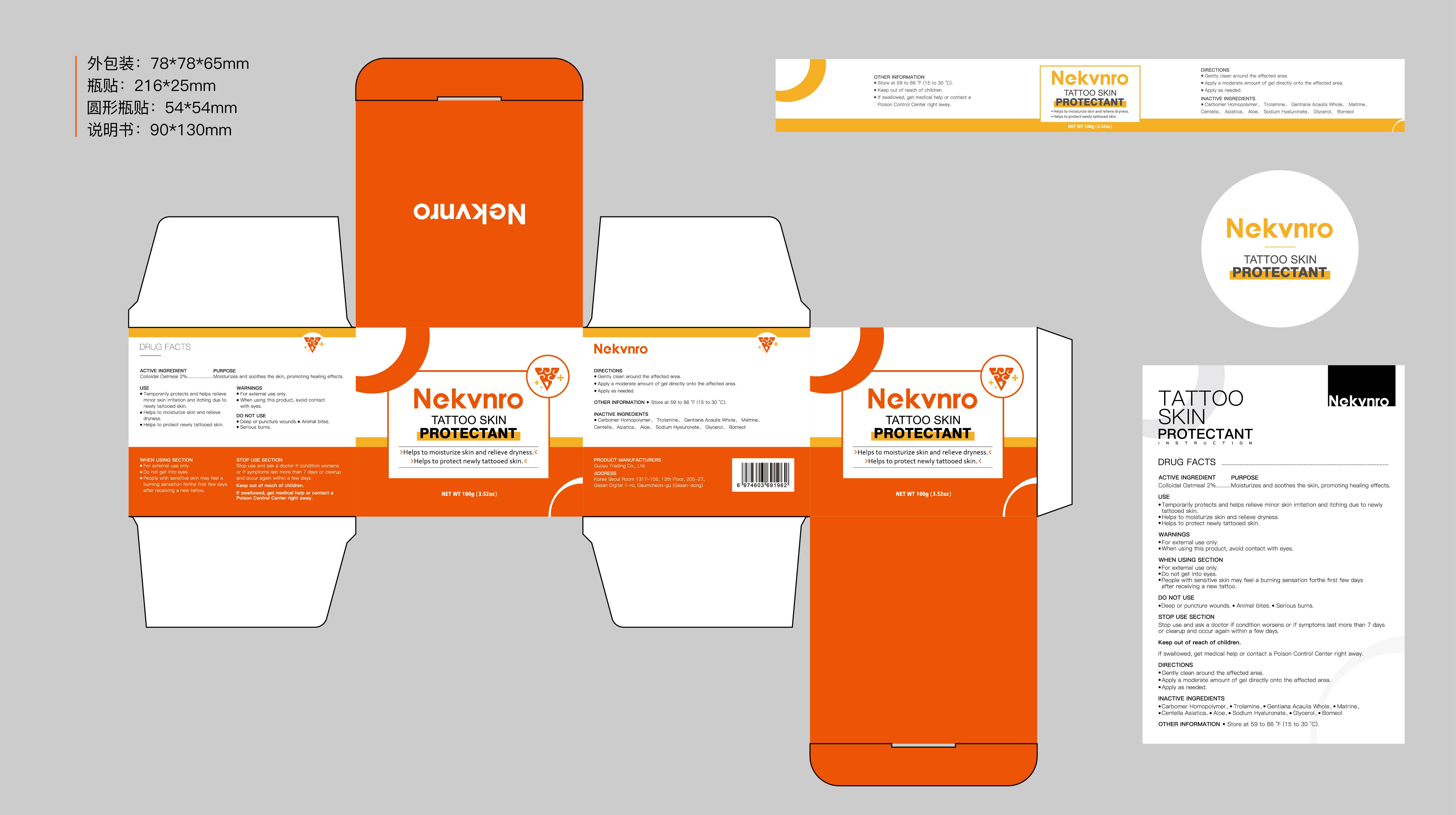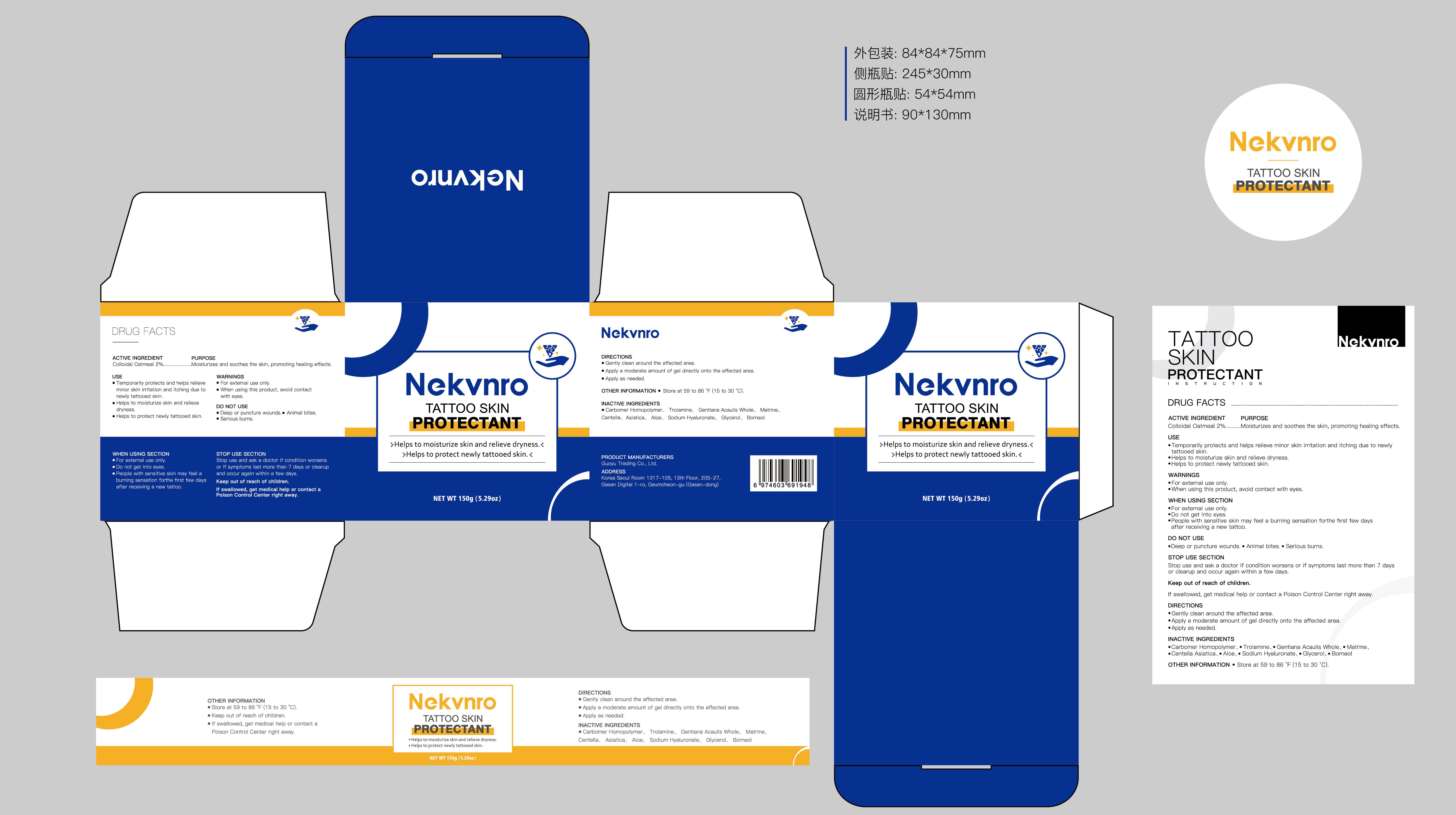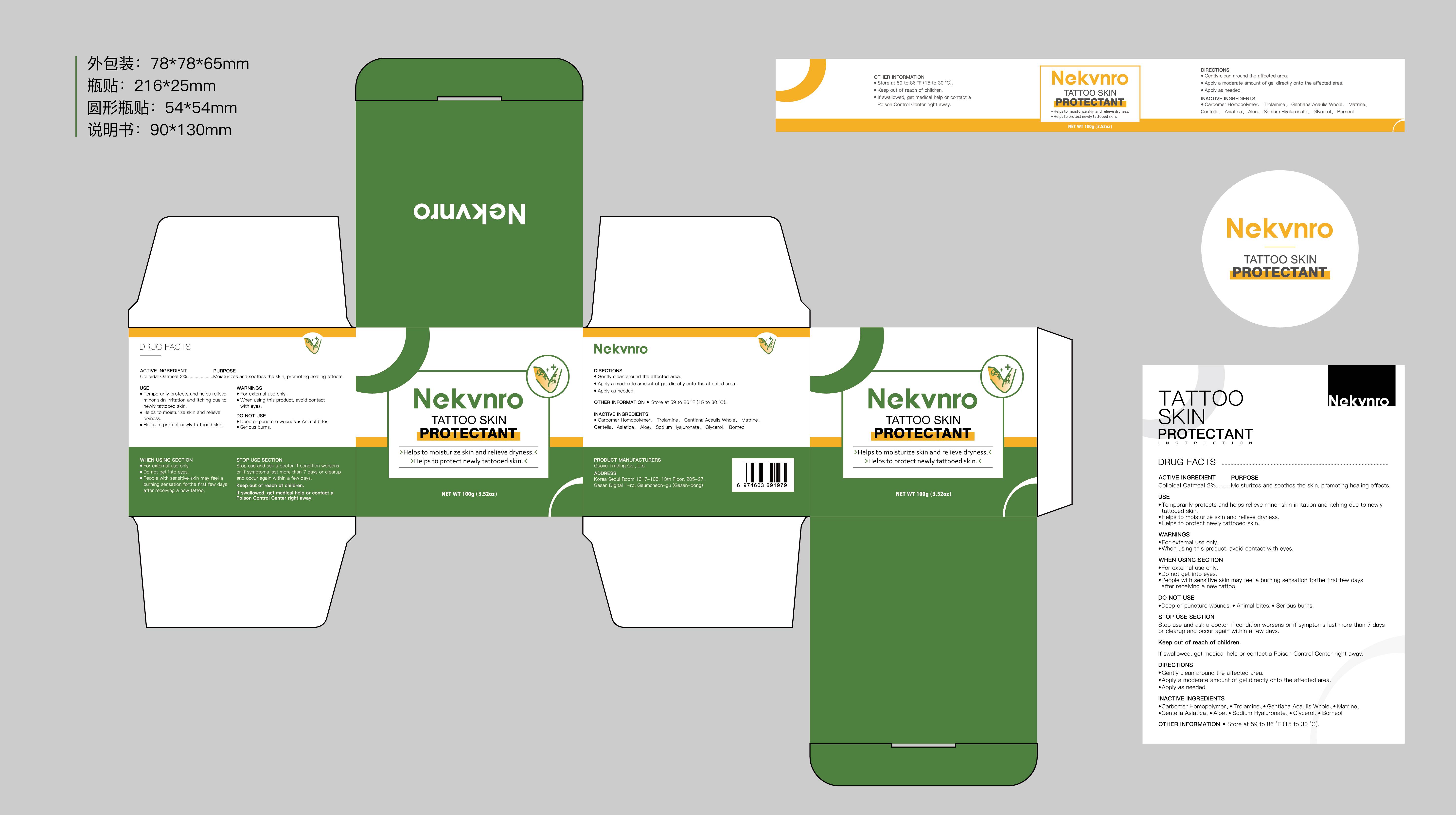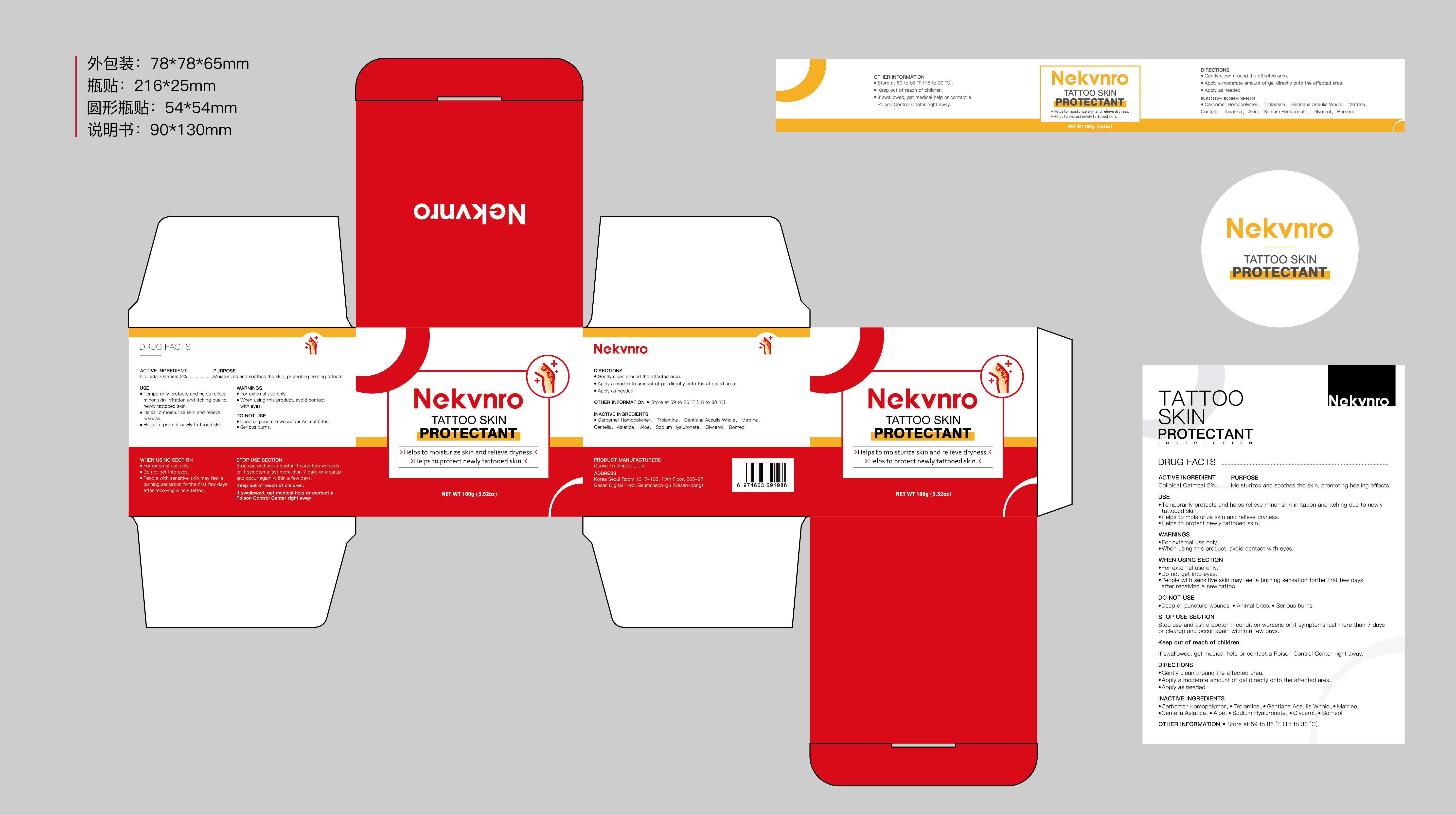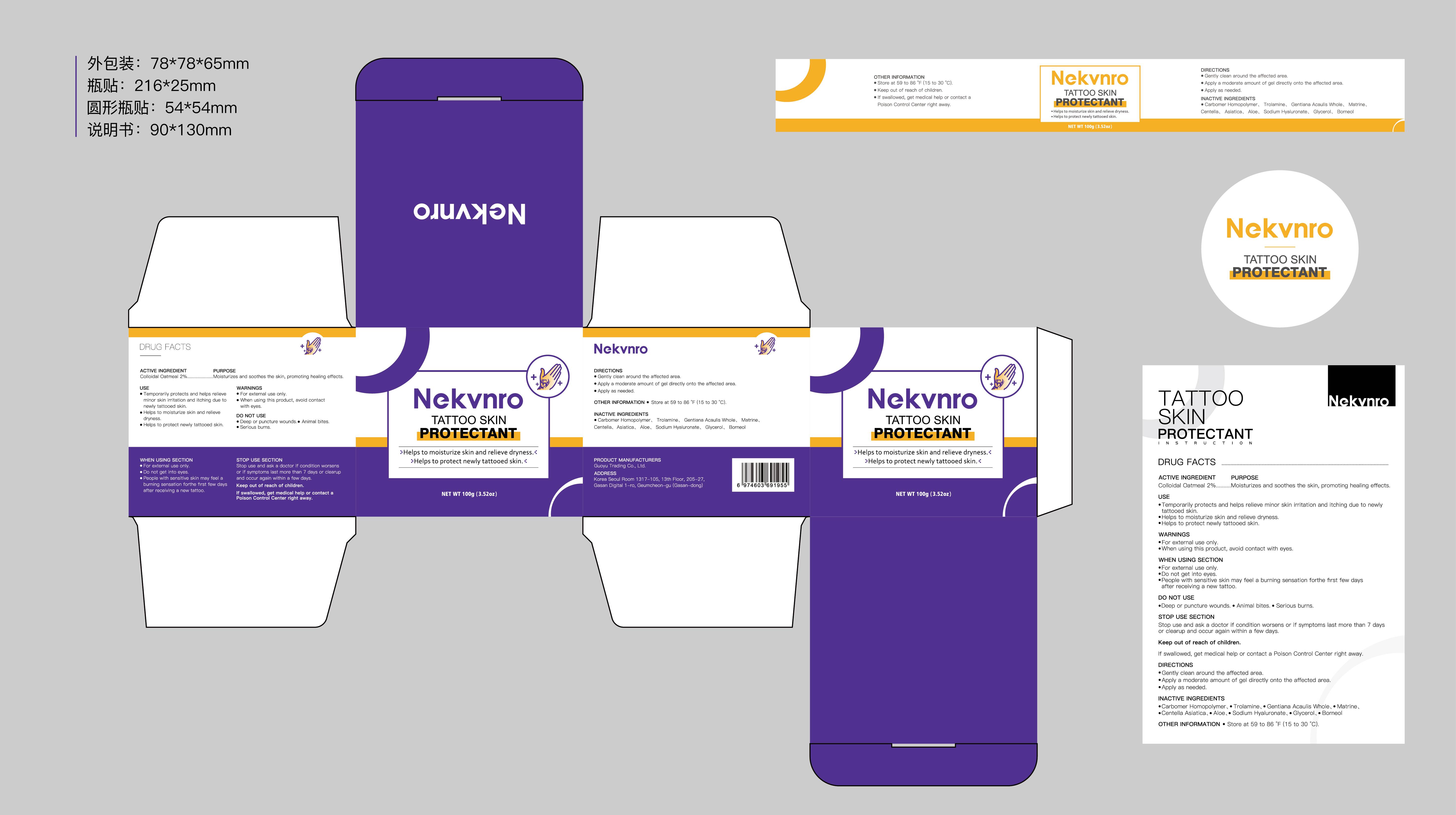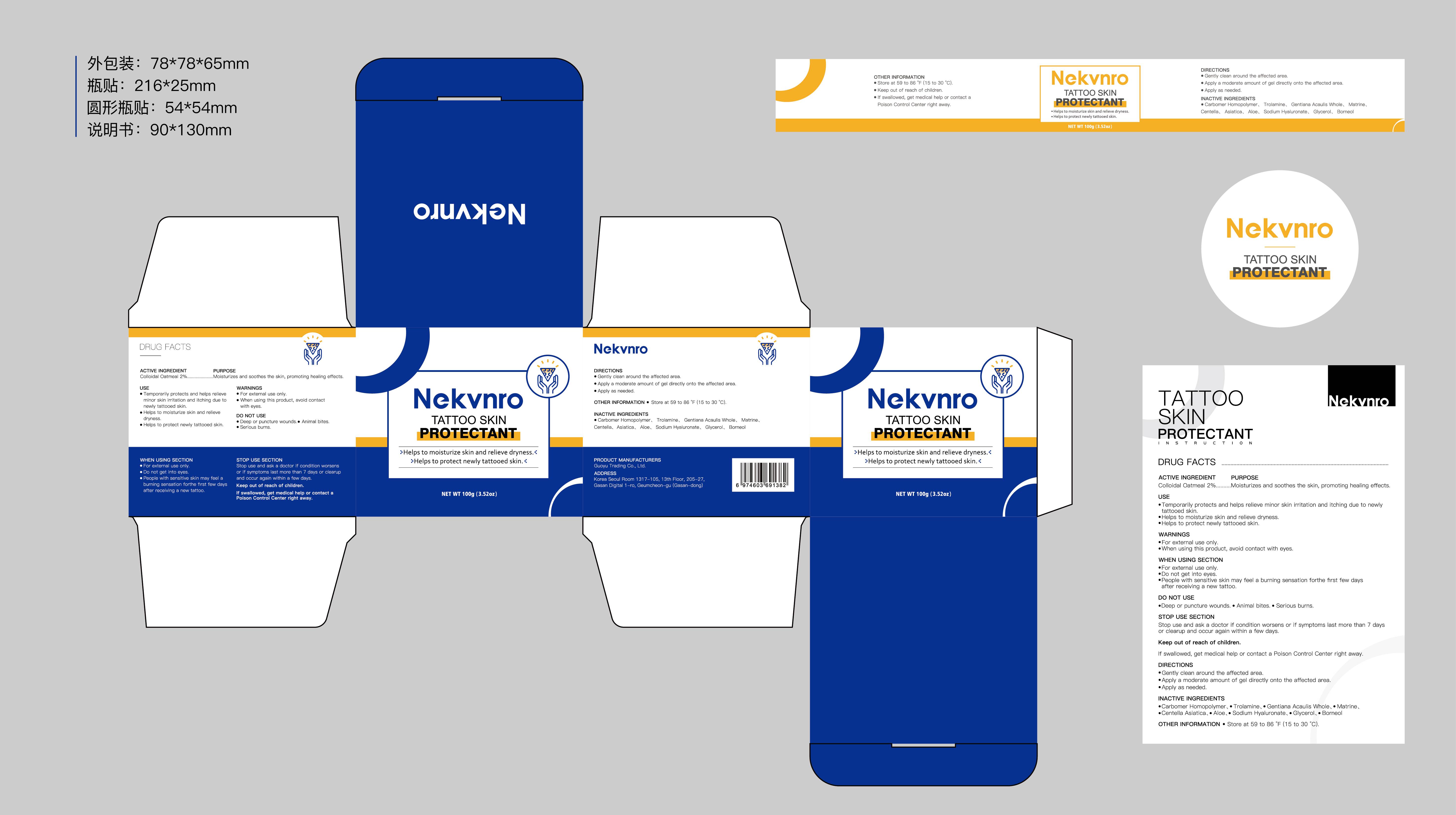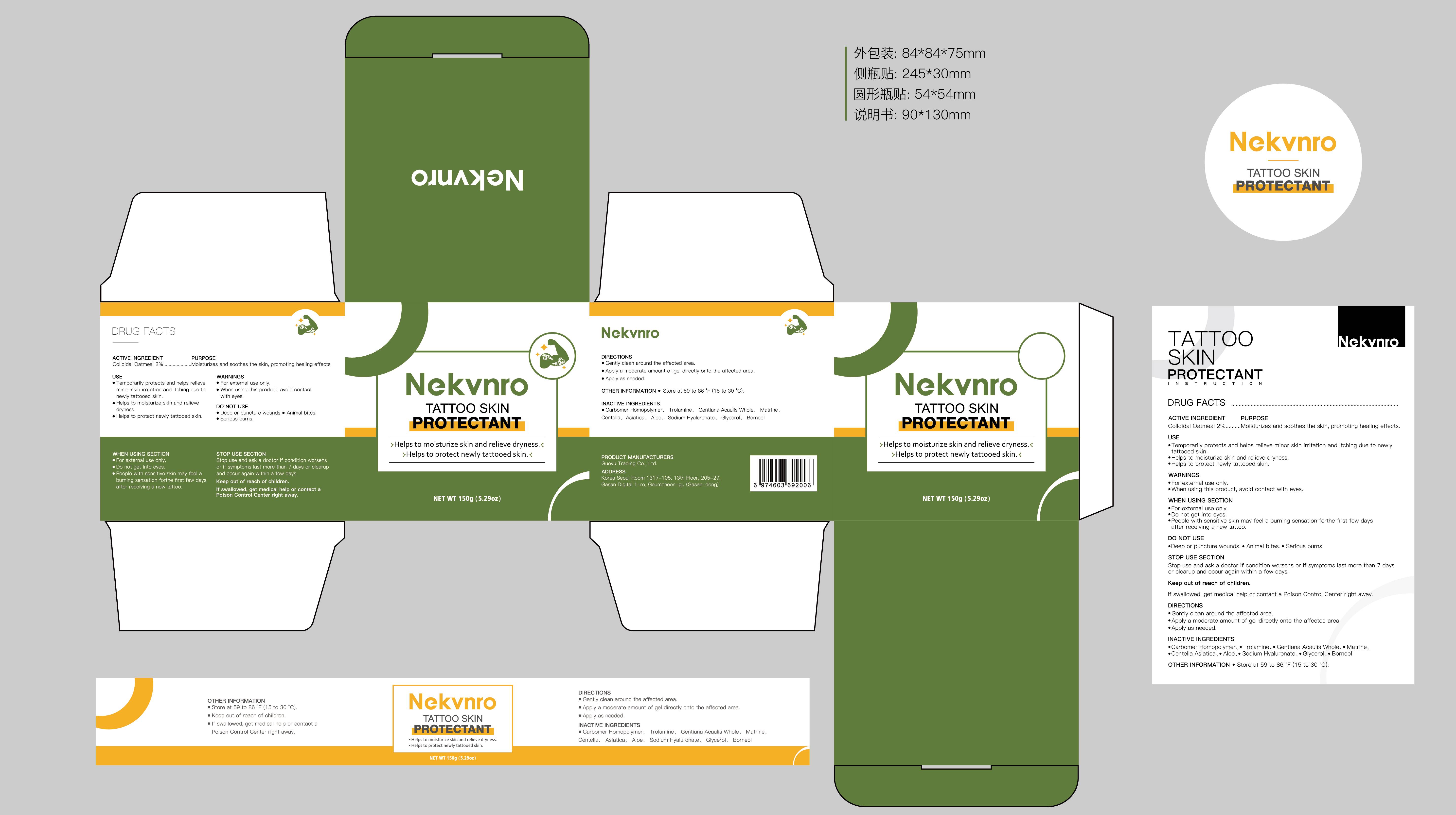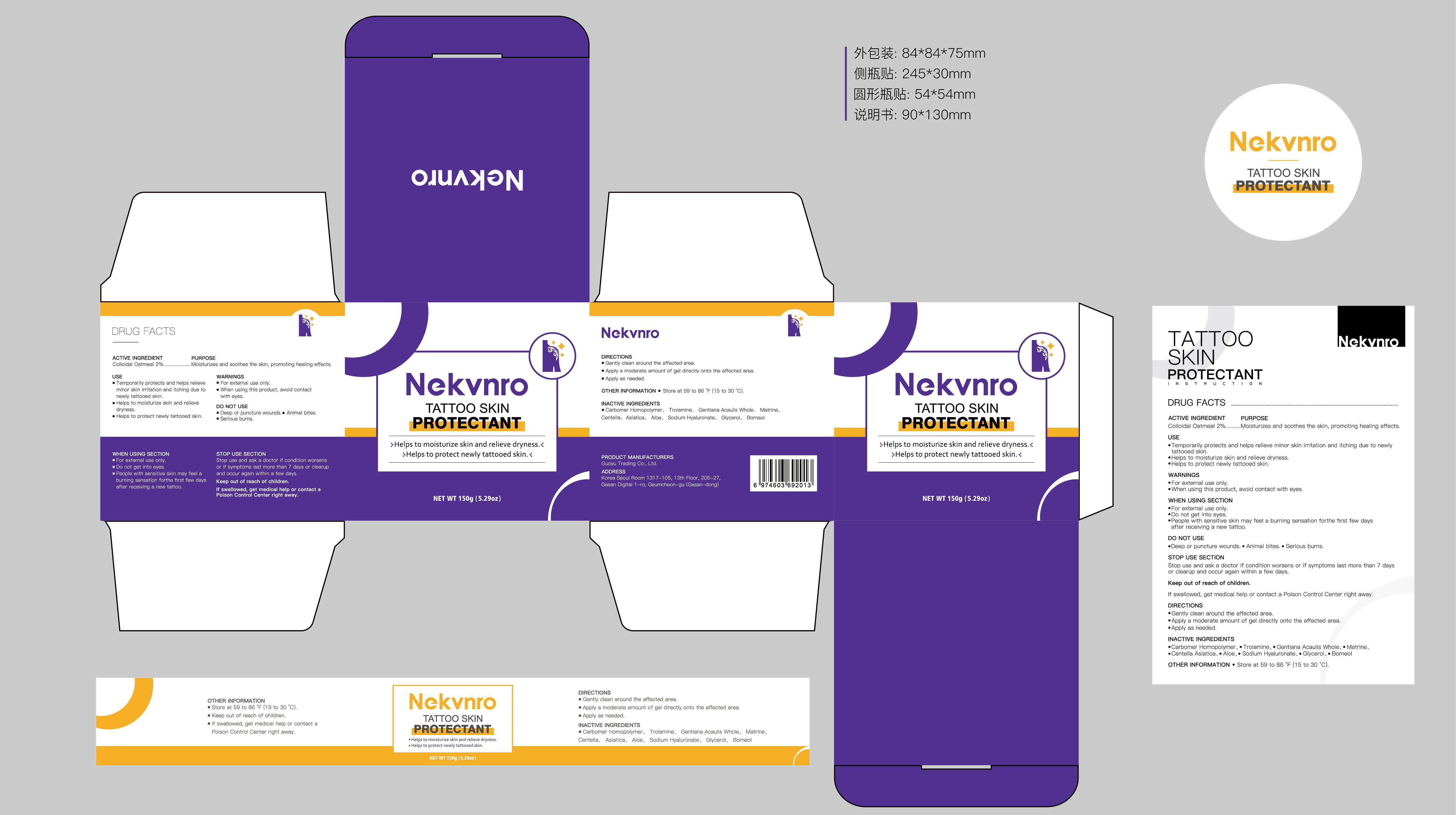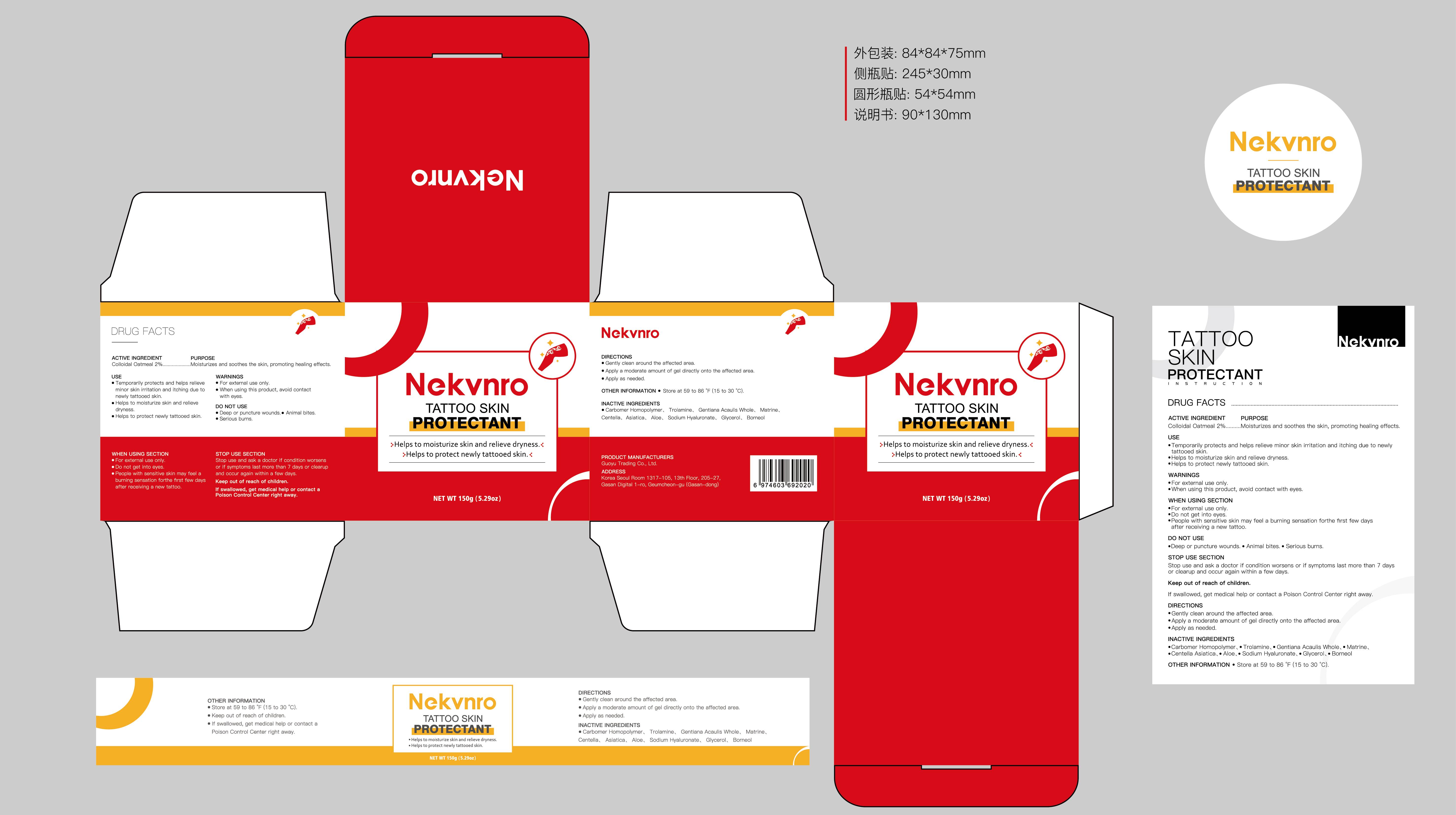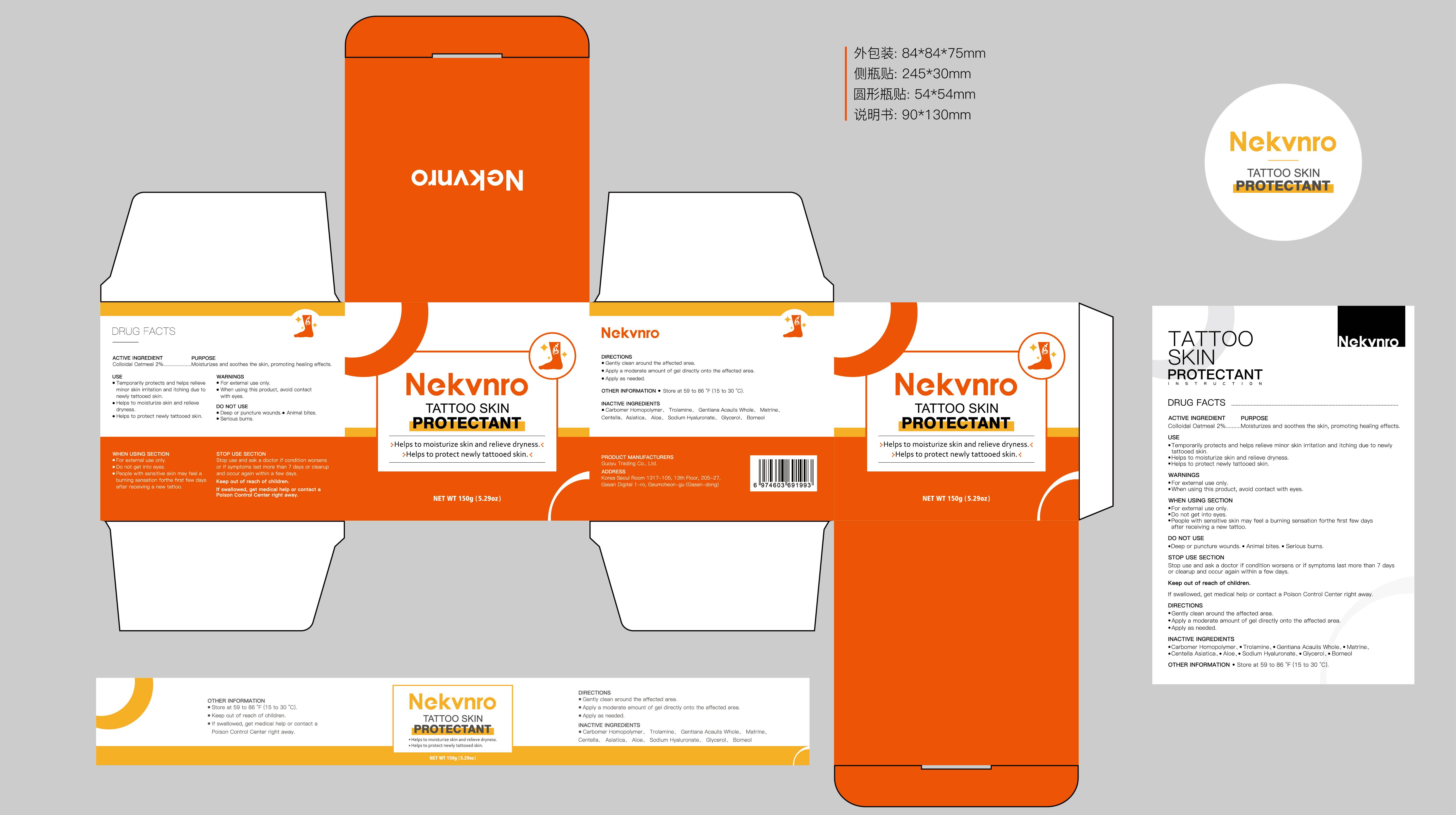 DRUG LABEL: Nekvnro Tattoo Skin Protectant
NDC: 84844-014 | Form: CREAM
Manufacturer: Guoyu Trading Co., Ltd.
Category: otc | Type: HUMAN OTC DRUG LABEL
Date: 20241114

ACTIVE INGREDIENTS: COLLOIDAL OATMEAL EXTRACT 2 g/100 g
INACTIVE INGREDIENTS: CENTELLA ASIATICA; GLYCERIN; CARBOMER HOMOPOLYMER, UNSPECIFIED TYPE; MATRINE; BORNEOL; TROLAMINE; GENTIANA ACAULIS WHOLE; ALOE; SODIUM HYALURONATE

84844-014

Active Ingredient

Colloidal Oatmeal 2%

Purpose

Moisturizes and soothes the skin, promoting healing effects.

Use

•Temporarily protects and helps relieve minor skin irritation and itching due to newly tattooed skin
• Helps to moisturize skin and relieve dryness
• Helps to protect newly tattooed skin ..

Warnings

• For external use only.
• When using this product, avoid contact with eyes.

Do not use

•Deep or puncture wounds. Animal bites. Serious burns.

When Using

•For external use only
•Do not get into eyes
•People with sensitive skin may feel a burning sensation forthe first few days after receiving a new tattoo.

Stop Use

Stop use and ask a doctor if condition worsens or if symptoms last more than 7 days or clearup and occur again within a few days.

Ask Doctor

Stop use and ask a doctor if condition worsens or if symptoms last more than 7 days or clearup and occur again within a few days.

Keep Oot Of Reach Of Children

If swallowed, get medical help or contact a Poison Control Center right away.

Directions

• Gently clean around the affected area.
• Apply a moderate amount of gel directly onto the affected area.
• Apply as needed.

Other information

• Store at 59 to 86 °F (15 to 30 °C).

Inactive ingredients

Carbomer Homopolymer Trolamine、Gentiana Acaulis Whole、Matrine、Centella Asiatica、Aloe、Sodium Hyaluronate、Glycerol、Borneol